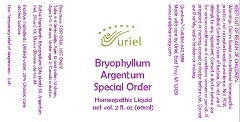 DRUG LABEL: Bryophyllum Argentum Special Order
NDC: 48951-2129 | Form: LIQUID
Manufacturer: Uriel Pharmacy Inc.
Category: homeopathic | Type: HUMAN OTC DRUG LABEL
Date: 20181002

ACTIVE INGREDIENTS: SILVER 6 [hp_X]/1 mL; KALANCHOE DAIGREMONTIANA LEAF 3 [hp_X]/1 mL; BOS TAURUS UTERUS 8 [hp_X]/1 mL
INACTIVE INGREDIENTS: ALCOHOL; WATER; LACTOSE, UNSPECIFIED FORM

Bryophyllum Argentum Special Order

INDICATIONS AND USAGE

Directions: FOR ORAL USE ONLY.

DOSAGE AND ADMINISTRATION

Take 3-4 times daily. Ages 12 and older: 10 drops. Ages 2-11: 5 drops. Under age 2: Consult a doctor.

ACTIVE INGREDIENT

Active Ingredients: Bryophyllum (Life plant) 3X, Argentum met. (Silver) 6X, Uterus (Bovine uterus) 8X

INACTIVE INGREDIENT

Inactive Ingredients: Distilled water, 20% Organic cane alcohol, Lactose

PURPOSE

Use: Temporary relief of sleeplessness.

KEEP OUT OF REACH OF CHILDREN.

WARNINGS

Warnings: Claims based on traditional homeopathic practice, not accepted medical evidence. Not FDA evaluated. Contains traces of lactose. Do not use if allergic to any ingredient. Consult a doctor before use for serious conditions or if conditions worsen or persist. If pregnant or nursing, consult a doctor before use. Do not use if safety seal is broken or missing.

Questions? Call 866.642.2858
Made with care by Uriel, East Troy, WI 53120
www.urielpharmacy.com